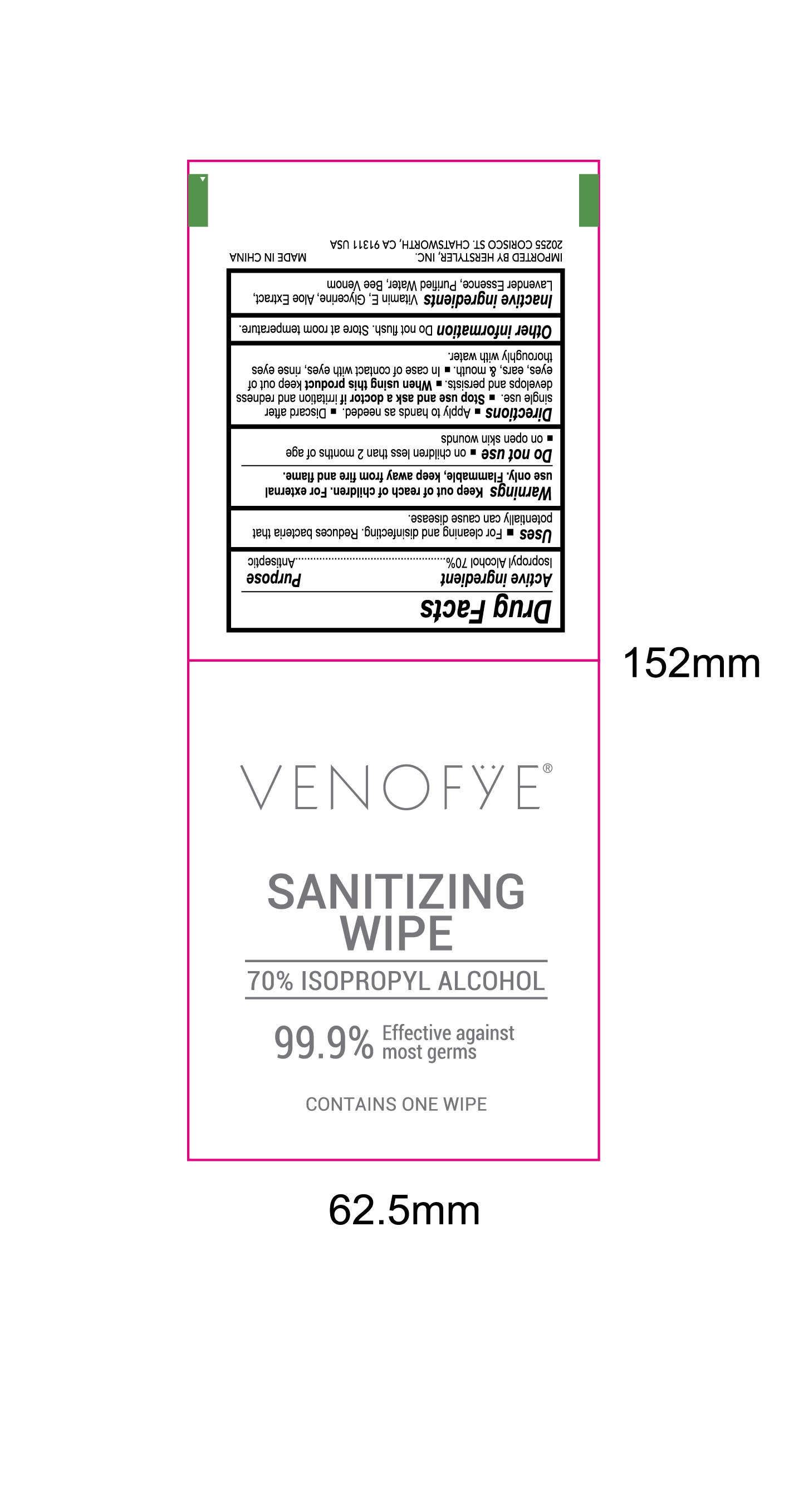 DRUG LABEL: VENOFYE Sanitizing Wipe
NDC: 75177-056 | Form: SOLUTION
Manufacturer: Herstyler, Inc.
Category: otc | Type: HUMAN OTC DRUG LABEL
Date: 20200525

ACTIVE INGREDIENTS: ISOPROPYL ALCOHOL 1.155 mL/1 1
INACTIVE INGREDIENTS: WATER; GLYCERIN; ALOE; .ALPHA.-TOCOPHEROL ACETATE; LAVENDER OIL

NA

Active Ingredient(s)

Isopropyl Alcohol 70%

Purpose

Antiseptic

Use

For cleaning and disinfecting. Reduce bacteria than potentially can cause disease

Warnings

For external use only.

Flammable. Keep away from fire and flame

Do not use on

- Children less than 2 months of age
- Open skin wounds

When using this product keep out of eyes, ears, and mouth. In case of contact with eyes, rinse eyes thoroughly with water.

Stop use and ask a doctor if irritation or redness develops and persists

Keep out of reach of children.

Directions

Apply to hands as needed

Discard after single use

Other information

Do not flush

Store at room temperature

Inactive ingredients

Water, Vitamin E, Glycerin, Aloe Extract, Lavender Essence, Bee Venom